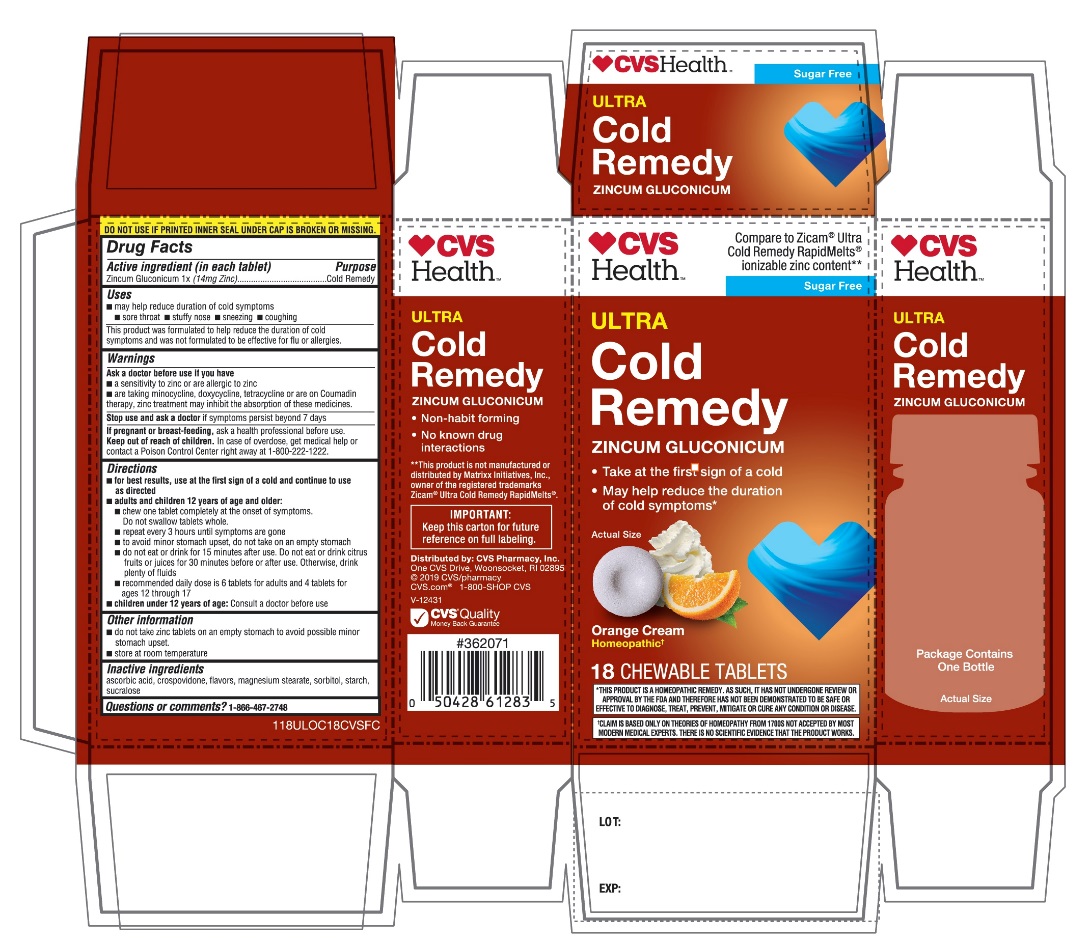 DRUG LABEL: CVS Health Cold Remedy

NDC: 69842-691 | Form: TABLET
Manufacturer: CVS PHARMACY, INC
Category: homeopathic | Type: HUMAN OTC DRUG LABEL
Date: 20251208

ACTIVE INGREDIENTS: ZINC GLUCONATE 1 [hp_X]/1 1
INACTIVE INGREDIENTS: ASCORBIC ACID; CROSPOVIDONE (120 .MU.M); MAGNESIUM STEARATE; SORBITOL; STARCH, CORN; SUCRALOSE

CVS Health™Zinc Tablets Orange Cream Flavor 18 Chewable Tablets

Drug Facts

Active Ingredient

Zincum Gluconicum 1x (14mg Zinc)

Purpose

Cold Remedy

Uses

- may help reduce duration of cold symptoms:
  - sore throat
  - stuffy nose
  - sneezing
  - coughing
- This product was formulated to help reduce the duration and severity of cold symptoms and was not formulated to be effective for flu or allergies.

Warnings

Ask a doctor before use if you have

- a sensitivity to zinc or are allergic zinc
- are taking minocycline, doxycycline, tetracycline or are on Coumadin therapy, zinc treatment may inhibit the absorption of these medicines.

Stop Use and ask a doctor

If symptoms persist beyond 7 days.

If pregnant or breast feeding

As ask health professional before use.

Keep Out of Reach of Children

In case of overdose, get medical help or contact a Poison Control Center right away at 1-800-222-1222.

Directions

- for best results, use at the first sign of a cold and continue to use as directed
- adults and children 12 years of age and older:
- chew one tablet completely at the onset of symptoms. Do not swallow tablets whole.
- repeat every 3 hours until symptoms are gone
- to avoid minor stomach upset, do not take on an empty stomach.
- do not eat or drink for 15 minutes after use. Do not eat or drink citrus fruits or juices for 30 minutes before or after use. Otherwise, drink plenty of fluids.
- recommended daily dose is 6 tablets for adults and 4 tablets for ages 12 through 17
- Children under 12 years of age:Consult a doctor before use.

Other information

- do not take zinc tablets on an empty stomach to avoid possible minor stomach upset.
- store at room temperature

Inactive ingredients

ascorbic acid, crospovidone, magnesium stearate, flavors, sorbitol, starch ,sucralose.

Questions or comments?

1-866-467-2748

PRINCIPAL DISPLAY PANEL

CVS Health™

NDC 69842-691-18

*Compare to Zicam®Cold Remedy RapidMelts®Ionizable Zinc Content**

SUGAR FREE

Non-Drowsy
ULTRA Cold Remedy

ZINCUM GLUCONICUM

- Take at the first sign of a cold
- May help reduce the duration of cold symptoms*
- Non-habit forming
- No known drug interactions

Orange Cream Flavor

Homeopathic†

18CHEWABLE TABLETS

Package Contains One Bottle

DO NOT USE IF PRINTED INNER SEAL UNDER CAP IS BROKEN OR MISSING.

†CLAIM IS BASED ONLY ON THEORIES OF HOMEOPATHY FROM 1700S NOT ACCEPTED BY MOST MODERN MEDICAL EXPERTS .THERE IS NO SCIENTIFIC EVIDENCE THAT THE PRODUCT WORKS

**THIS PRODUCT IS A HOMEOPATHIC REMEDY, AS SUCH, IT HAS NOT UNDERGONE REVIEW ON APPROVAL BY THE FDA AND THEREFORE HAS NOT BEEN DEMONSTRATED TO BE SAFE OR EFFECTIVE TO DIAGNOSE, TREAT, PREVENT, MITIGATE OR CURE ANY CONDITION OR DISEASE.

IMPORTANT: Keep this carton for future reference on full labeling.

*This product is not manufactured or distributed by Matrixx Initiatives, Inc., owner of the registered trademarks Zicam®Cold Remedy Rapidmelts®
Distributed by:

CVS Pharmacy, Inc.

One CVS Drive

Woonsocket, RI 02895

© 2019 CVS/pharmacy

CVS.com®1-800-SHOP CVS

V-12431

CVS Quality Money Back Guarantee